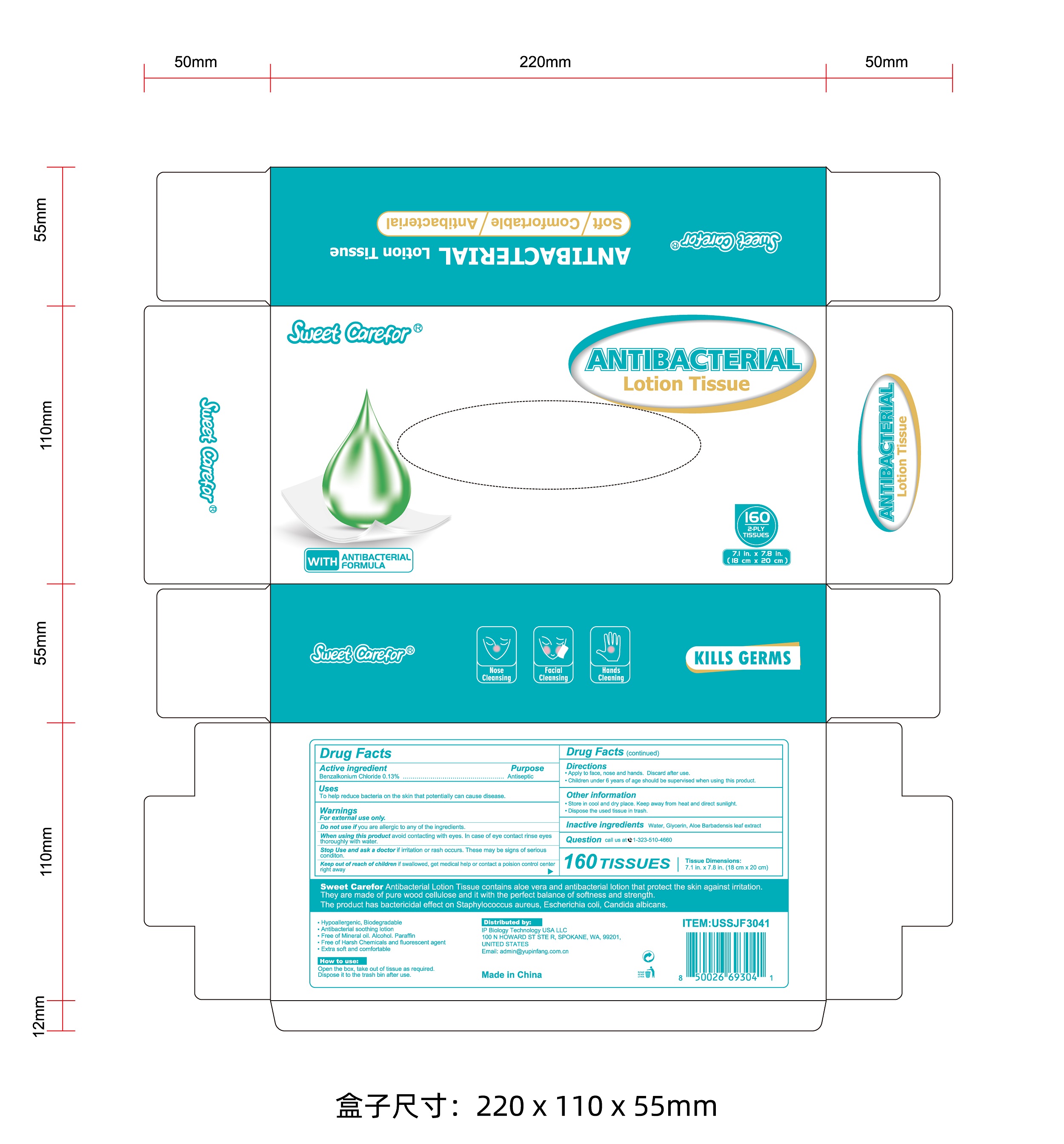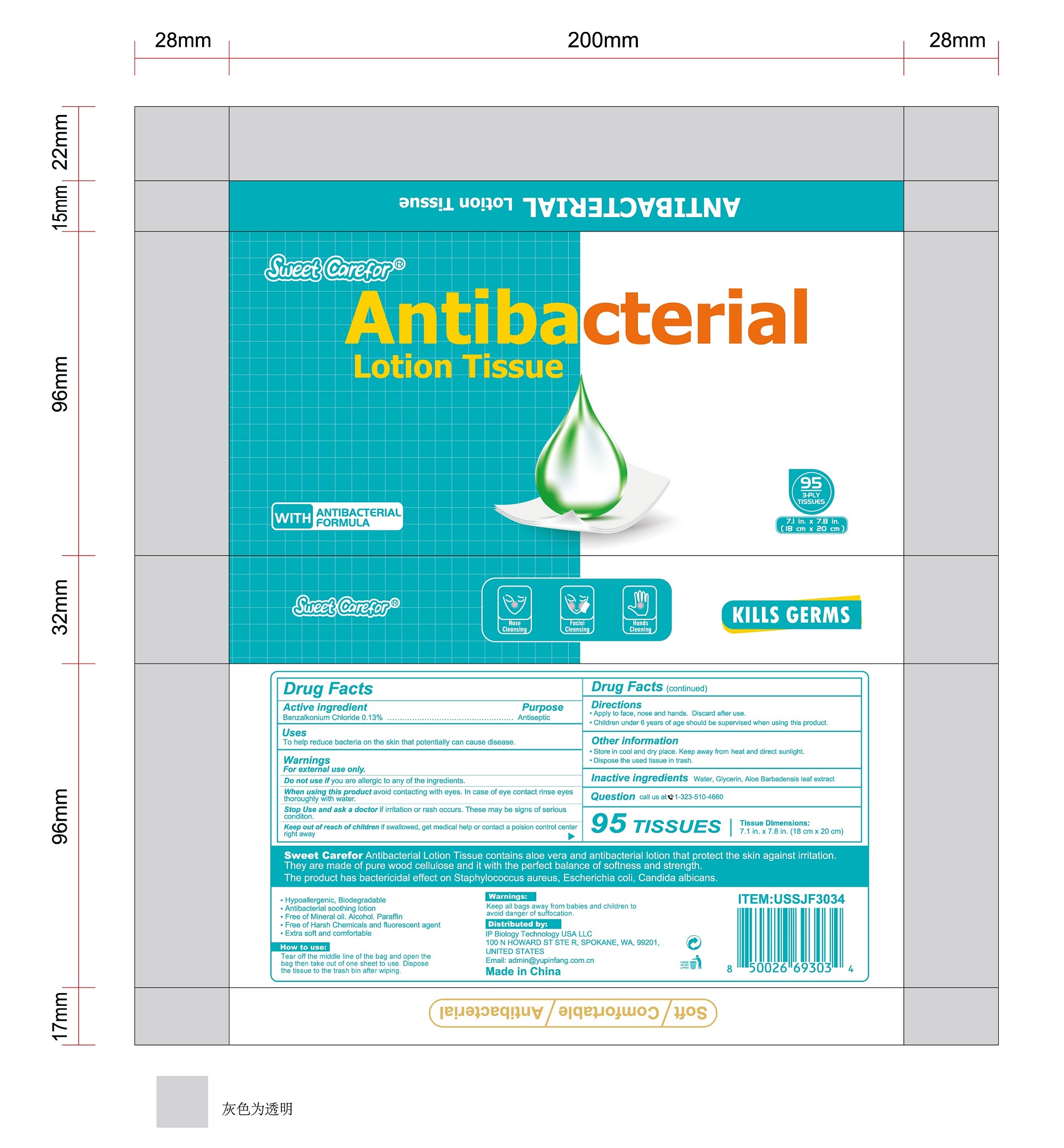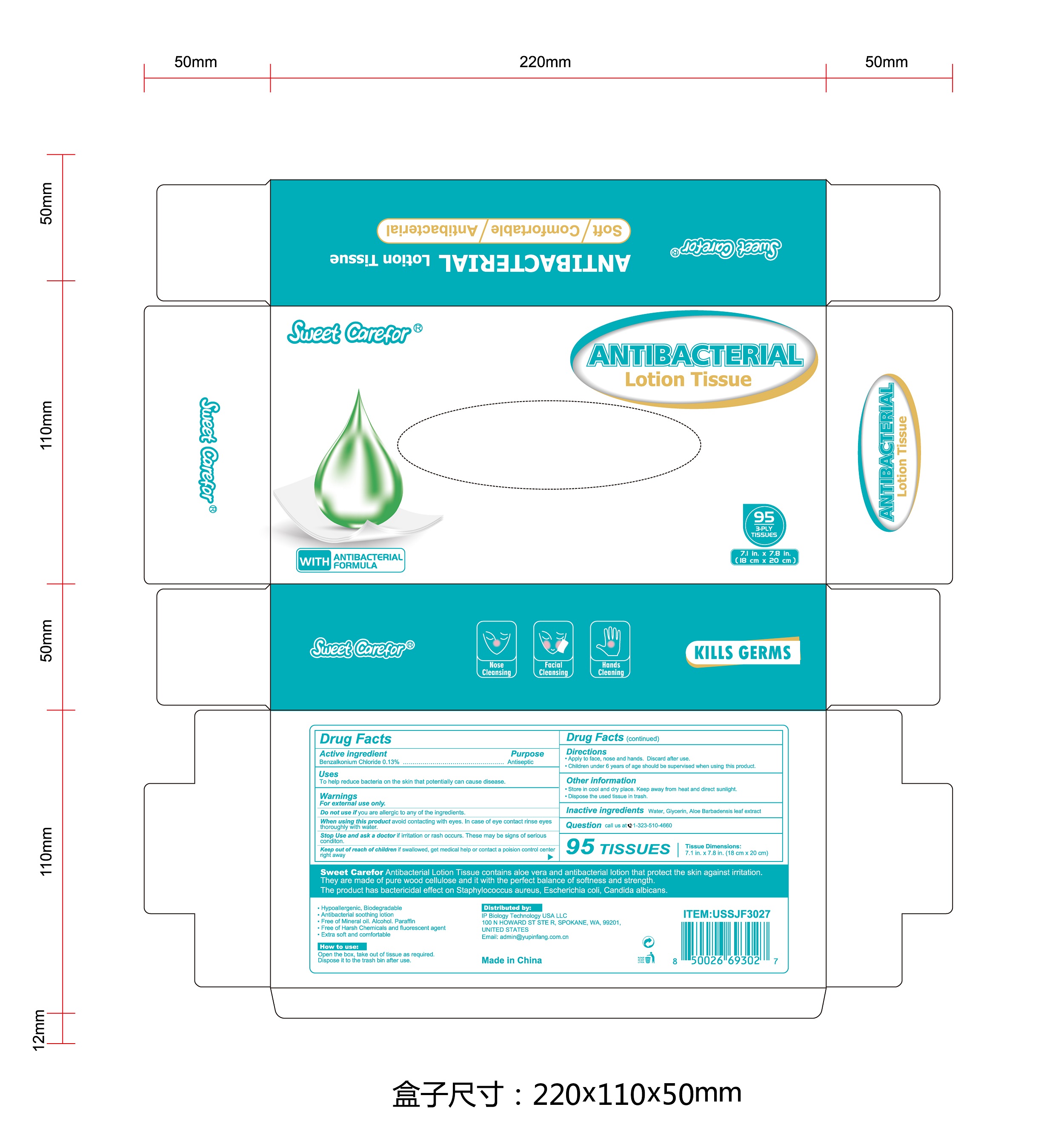 DRUG LABEL: Antibacterial LotionTissue
NDC: 52489-003 | Form: CLOTH
Manufacturer: Imperial Palace Commodity (shenzhen) Co., Ltd
Category: otc | Type: HUMAN OTC DRUG LABEL
Date: 20231120

ACTIVE INGREDIENTS: BENZALKONIUM CHLORIDE 1.3 mg/1 mL
INACTIVE INGREDIENTS: GLYCERIN; WATER; ALOE VERA LEAF

Antibacterial Lotion Tissue

DRUG FACTS

Active Ingredient(s)

Benzalkonium chloride 0.13%

Purpose

Antiseptic

Use

To help reduce bacteria on the skin that potentially can cause disease.

Warnings

For external use only.

Do not use if you are allergic to any of the ingredients.

When using this product avoid contacting with eyes. In case of eye contact rinse eyes thoroughly with water.

Stop Use and ask a doctor if irritation or rash occurs. These may be signs of serious condition.

Keep out of reach of children if swallowed,get medical help or contact a poison control center right away.

Directions

Apply to face, nose and hands. Discard after use.

Children under 6 years of age should be supervised when using this product.

How to uses

Bag

Tear off the middle line of the bag and open the bag then take out of one sheet to use.Dispose the tissue to the trash bin after wiping.

Box

Open the box, take out of tissue as required.

Dispose it to the trash bin after use.

Inactive ingredients

Water, Glycerin, Aloe Barbadensis leaf extract.

Package Label - Principal Display Panel

NDC:52489-003-01

NDC:52489-003-02

NDC:52489-003-03